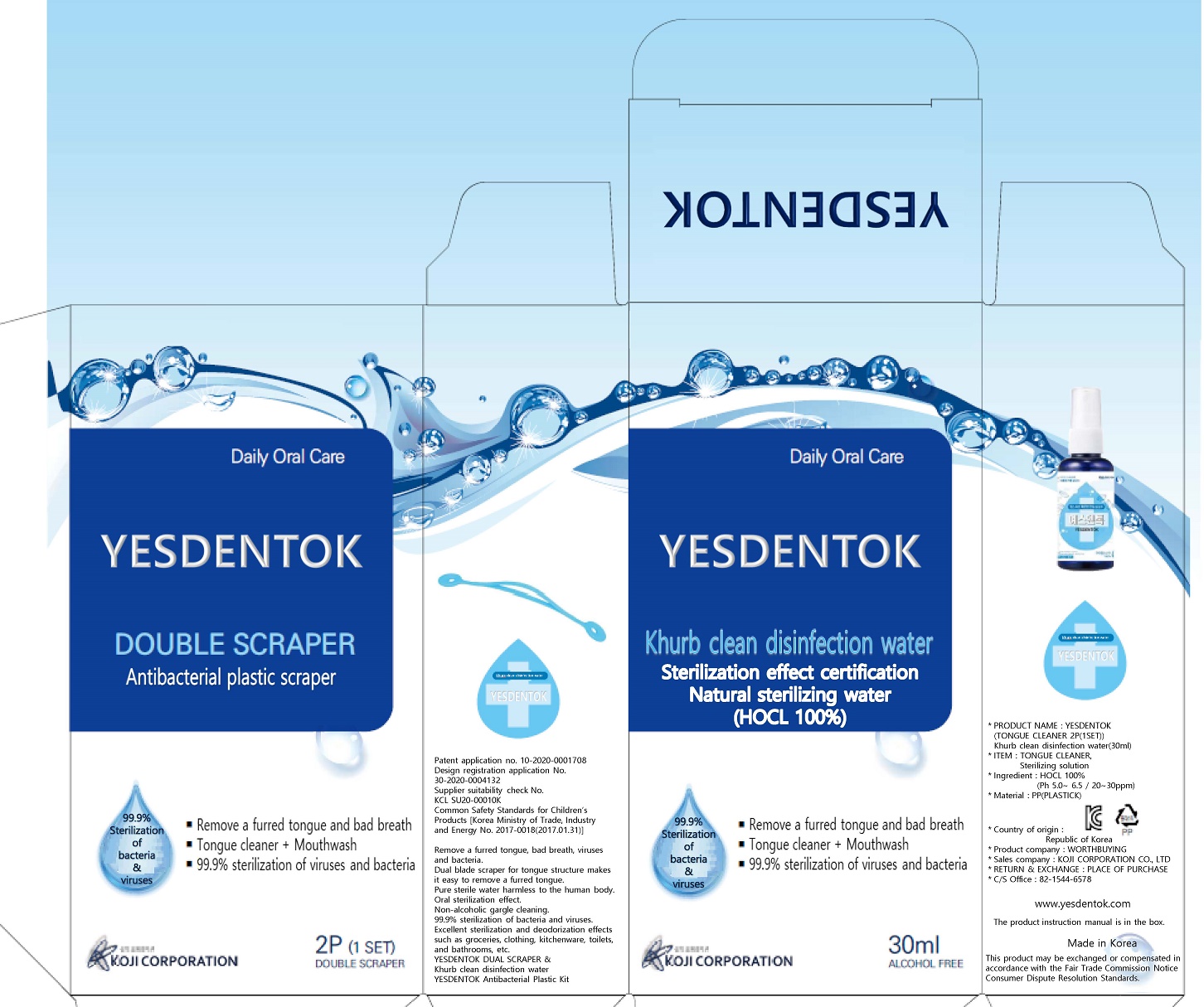 DRUG LABEL: YESDENTOK Khurb clean disinfection water
NDC: 80703-0001 | Form: LIQUID
Manufacturer: KOJI CORPORATION Co., Ltd
Category: otc | Type: HUMAN OTC DRUG LABEL
Date: 20201016

ACTIVE INGREDIENTS: HYPOCHLOROUS ACID 100 g/100 mL
INACTIVE INGREDIENTS: WATER

Drug Facts

ACTIVE INGREDIENT

HOCL

PURPOSE

For hand washing and tongue cleaner to decrease bacteria on the skin and scraper

KEEP OUT OF REACH OF THE CHILDREN

INDICATIONS AND USAGE

pump a small amount of product into palm of hand, mouth and scraper.

Rub thoroughly over all surfaces of both hands for 15 seconds.

After using tongue cleaner, spray evenly on the mouth and spit out about 15 seconds later.

WARNINGS

■ For external use only.

■ Do not use in eyes.

■ lf swallowed, get medical help promptly.

■ Stop use, ask doctor lf irritation occurs.

■ Keep out of reach of children.

DOSAGE AND ADMINISTRATION

for external use only

INACTIVE INGREDIENT

water